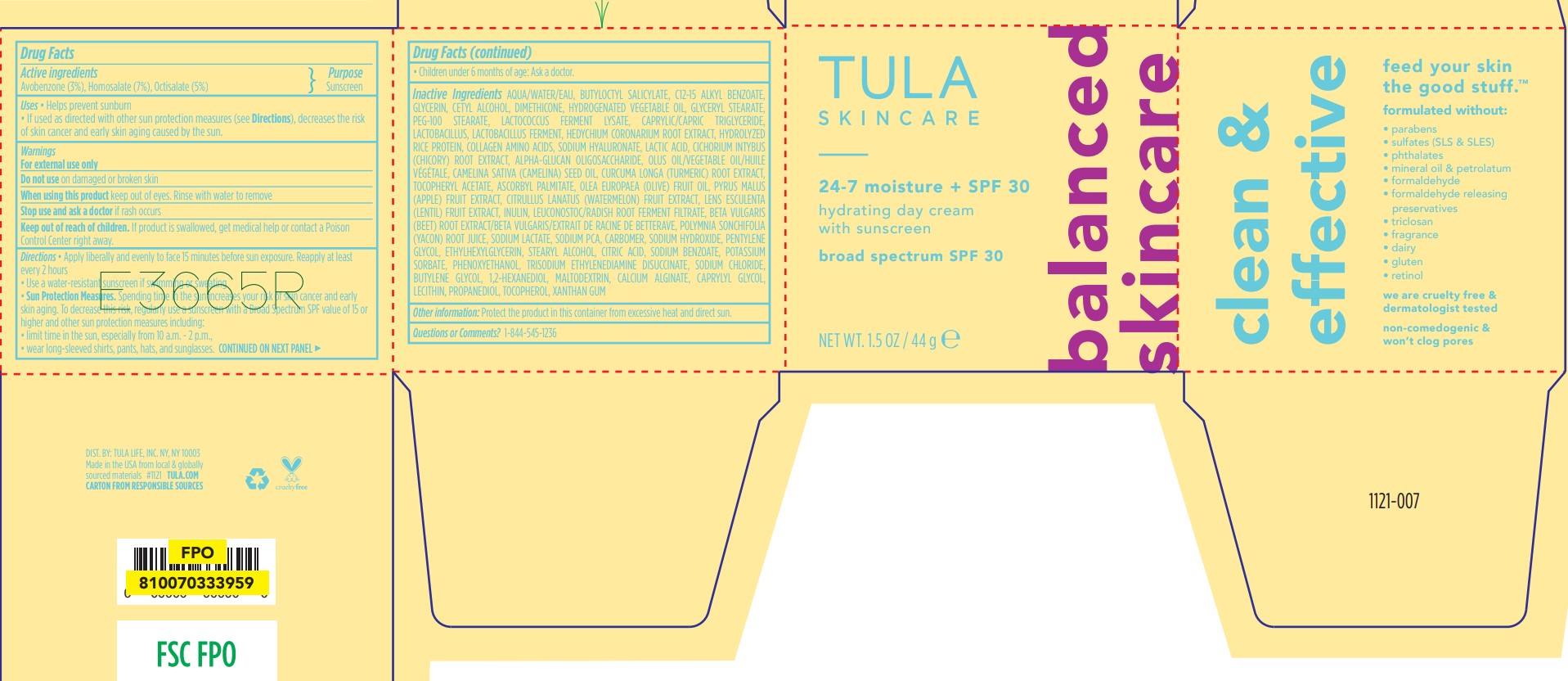 DRUG LABEL: Tula 24-7 Moisture Plus SPF 30 Hydrating Day with Sunscreen
NDC: 59735-105 | Form: CREAM
Manufacturer: Mana Products,Inc
Category: otc | Type: HUMAN OTC DRUG LABEL
Date: 20250708

ACTIVE INGREDIENTS: OCTISALATE 5 g/100 g; AVOBENZONE 3 g/100 g; HOMOSALATE 7 g/100 g
INACTIVE INGREDIENTS: WATERMELON; .ALPHA.-GLUCAN OLIGOSACCHARIDE; LACTIC ACID; VICIA LENS FRUIT; CALCIUM ALGINATE; CAMELINA SATIVA SEED OIL; LEUCONOSTOC/RADISH ROOT FERMENT FILTRATE; MALTODEXTRIN; TOCOPHEROL; SODIUM HYALURONATE; WATER; GLYCERIN; DIMETHICONE; PEG-100 STEARATE; CETYL ALCOHOL; STEARYL ALCOHOL; CAPRYLYL GLYCOL; 1,2-HEXANEDIOL; PHENOXYETHANOL; XANTHAN GUM; PYRUS MALUS (APPLE) FRUIT; SODIUM CHLORIDE; BUTYLENE GLYCOL; BUTYLOCTYL SALICYLATE; C12-15 ALKYL BENZOATE; CHICORY ROOT; CITRIC ACID; POTASSIUM SORBATE; HYDROLYZED RICE PROTEIN (ENZYMATIC; 2000 MW); CAPRYLIC/CAPRIC TRIGLYCERIDE; CARBOMER; INULIN; BEET; ETHYLHEXYLGLYCERIN; GLYCERYL STEARATE; HEDYCHIUM CORONARIUM ROOT; LACTOBACILLUS; ASCORBYL PALMITATE; LECITHIN, SOYBEAN; OLEA EUROPAEA (OLIVE) FRUIT OIL; PENTYLENE GLYCOL; POLYMNIA SONCHIFOLIA ROOT JUICE; PROPANEDIOL; SODIUM BENZOATE; SODIUM HYDROXIDE; SODIUM LACTATE; SODIUM PCA; ALPHA-TOCOPHEROL ACETATE; TRISODIUM ETHYLENEDIAMINE DISUCCINATE; CURCUMA LONGA (TURMERIC) ROOT

Tula 24-7 Moisture Plus SPF 30 Hydrating Day with Sunscreen Broad Spectrum SPF 30

Drug Facts

ACTIVE INGREDIENT

AVOBENZONE 3%

HOMOSALATE 7%

OCTISALATE 5%

PURPOSE

Sunscreen

Sunscreen

Sunscreen

Sunscreen

Uses

- helps prevent sunburn
- if used as directed with other sun protection measures (see Directions), decreases the risk of skin cancer and early skin aging caused by the sun

Warnings

For external use only

Do not use

- on damaged or broken skin

When using this product

- keep out of eyes. Rinse with water to remove.

Stop use and ask a doctor if

- rash occurs

Keep out of reach of children.If product is swallowed, get medical help or contact a Poison Control Center right away.

Directions

- apply liberally 15 minutes before sun exposure
- reapply at least every 2 hours
- use water resistant sunscreen if swimming or sweating
- Sun Protection Measures.Spending time in the sun increases your risk of skin cancer and early skin aging. To decrease this risk, regularly use a sunscreen with a Broad Spectrum SPF value of 15 or higher and other sun protection measures including:
  - limit time in sun, especially from 10 a.m. - 2 p.m.
  - wear long-sleeved shirts, pants, hats, and sunglasses
- children under 6 months: ask a doctor

Other information

- protect this product from excessive heat and direct sun

Inactive ingredients

WATER, BUTYLOCTYL SALICYLATE, C12-15 ALKYL BENZOATE, GLYCERIN, CETYL ALCOHOL, DIMETHICONE, HYDROGENATED VEGETABLE OIL, GLYCERYL STEARATE, PEG-100 STEARATE, LACTOCOCCUS FERMENT LYSATE, CAPRYLIC/CAPRIC TRIGLYCERIDE, LACTOBACILLUS, LACTOBACILLUS FERMENT, HEDYCHIUM CORONARIUM ROOT EXTRACT, HYDROLYZED RICE PROTEIN, COLLAGEN AMINO ACIDS, SODIUM HYALURONATE, LACTIC ACID, CICHORIUM INTYBUS (CHICORY) ROOT EXTRACT, ALPHA-GLUCAN OLIGOSACCHARIDE, OLUS OIL/VEGETABLE OIL/HUILE VÉGÉTALE, CAMELINA SATIVA (CAMELINA) SEED OIL, CURCUMA LONGA (TURMERIC) ROOT EXTRACT, TOCOPHERYL ACETATE, ASCORBYL PALMITATE, OLEA EUROPAEA (OLIVE) FRUIT OIL, PYRUS MALUS (APPLE) FRUIT EXTRACT, CITRULLUS LANATUS (WATERMELON) FRUIT EXTRACT, LENS ESCULENTA (LENTIL) FRUIT EXTRACT, INULIN, LEUCONOSTOC/RADISH ROOT FERMENT FILTRATE, BETA VULGARIS (BEET) ROOT EXTRACT/BETA VULGARIS/EXTRAIT DE RACINE DE BETTERAVE, POLYMNIA SONCHIFOLIA (YACON) ROOT JUICE, SODIUM LACTATE, SODIUM PCA, CARBOMER, SODIUM HYDROXIDE, PENTYLENE GLYCOL, ETHYLHEXYLGLYCERIN, STEARYL ALCOHOL, CITRIC ACID, SODIUM BENZOATE, POTASSIUM SORBATE, PHENOXYETHANOL, TRISODIUM ETHYLENEDIAMINE DISUCCINATE, SODIUM CHLORIDE, BUTYLENE GLYCOL, 1,2-HEXANEDIOL, MALTODEXTRIN, CALCIUM ALGINATE, CAPRYLYL GLYCOL, LECITHIN, PROPANEDIOL, TOCOPHEROL, XANTHAN GUM

Questions or comments?

Call 1-844-545-1236

Distr. by : TULA LIFE, INC. NY, NY 10003

PRINCIPAL DISPLAY PANEL - 44 g CARTON

TULA

SKINCARE

24-7 moisture + SPF 30

hydrating day cream

with sunscreen

BROAD SPECTRUM SPF 30

44 g (1.5 OZ)